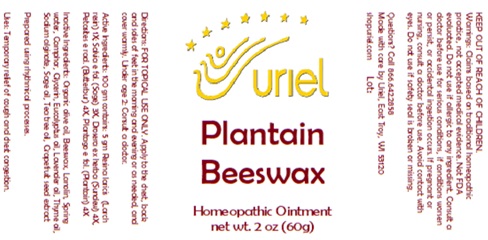 DRUG LABEL: Plantain Beeswax
NDC: 48951-8419 | Form: OINTMENT
Manufacturer: Uriel Pharmacy Inc.
Category: homeopathic | Type: HUMAN OTC DRUG LABEL
Date: 20250107

ACTIVE INGREDIENTS: PETASITES HYBRIDUS ROOT 4 [hp_X]/1 g; LARIX DECIDUA RESIN 1 [hp_X]/1 g; SAGE 3 [hp_X]/1 g; DROSERA ROTUNDIFOLIA 4 [hp_X]/1 g; PLANTAGO MAJOR LEAF 4 [hp_X]/1 g
INACTIVE INGREDIENTS: OLIVE OIL; YELLOW WAX; LANOLIN; WATER; CAMPHOR (NATURAL); GLYCERIN; EUCALYPTUS OIL; LAVENDER OIL; THYME OIL; SODIUM ALGINATE; TEA TREE OIL; SAGE OIL; CITRUS PARADISI SEED

Plantain Beeswax

INDICATIONS AND USAGE

Directions: FOR TOPICAL USE ONLY.

DOSAGE AND ADMINISTRATION

Apply to the chest, back and soles of feet in the morning and evening or as needed, and cover warmly. Under age 2: Consult a doctor.

ACTIVE INGREDIENT

Active Ingredients: 100 gm contains: 50 gm Resina laricis (Larch resin) 1X; Salvia e fol. (Sage) 3X, Drosera ex herba (Sundew) 4X, Petasites e rad. (Butterbur) 4X, Plantago e fol. (Plantain) 4X

INACTIVE INGREDIENT

Inactive Ingredients: Organic olive oil, Beeswax, Lanolin, Spring water, Camphor, Glycerin, Eucalyptus oil, Lavender oil, Thyme oil, Sodium alginate, Sage oil, Tea tree, Grapefruit seed extract

Prepared using rhythmical processes.

PURPOSE

Uses: Temporary relief of cough and chest congestion.

KEEP OUT OF REACH OF CHILDREN.

WARNINGS

Warnings: Claims based on traditional homeopathic practice, not accepted medical evidence. Not FDA evaluated. Do not use if allergic to any ingredient. Consult a doctor before use for serious conditions, if conditions worsen or persist, or accidental ingestion occurs. If pregnant or nursing, consult a doctor before use. Avoid contact with eyes. Do not use if safety seal is broken or missing.

QUESTIONS

Questions? Call 866.642.2858 Made with care by Uriel, East Troy, WI 53120 shopuriel.com Lot: